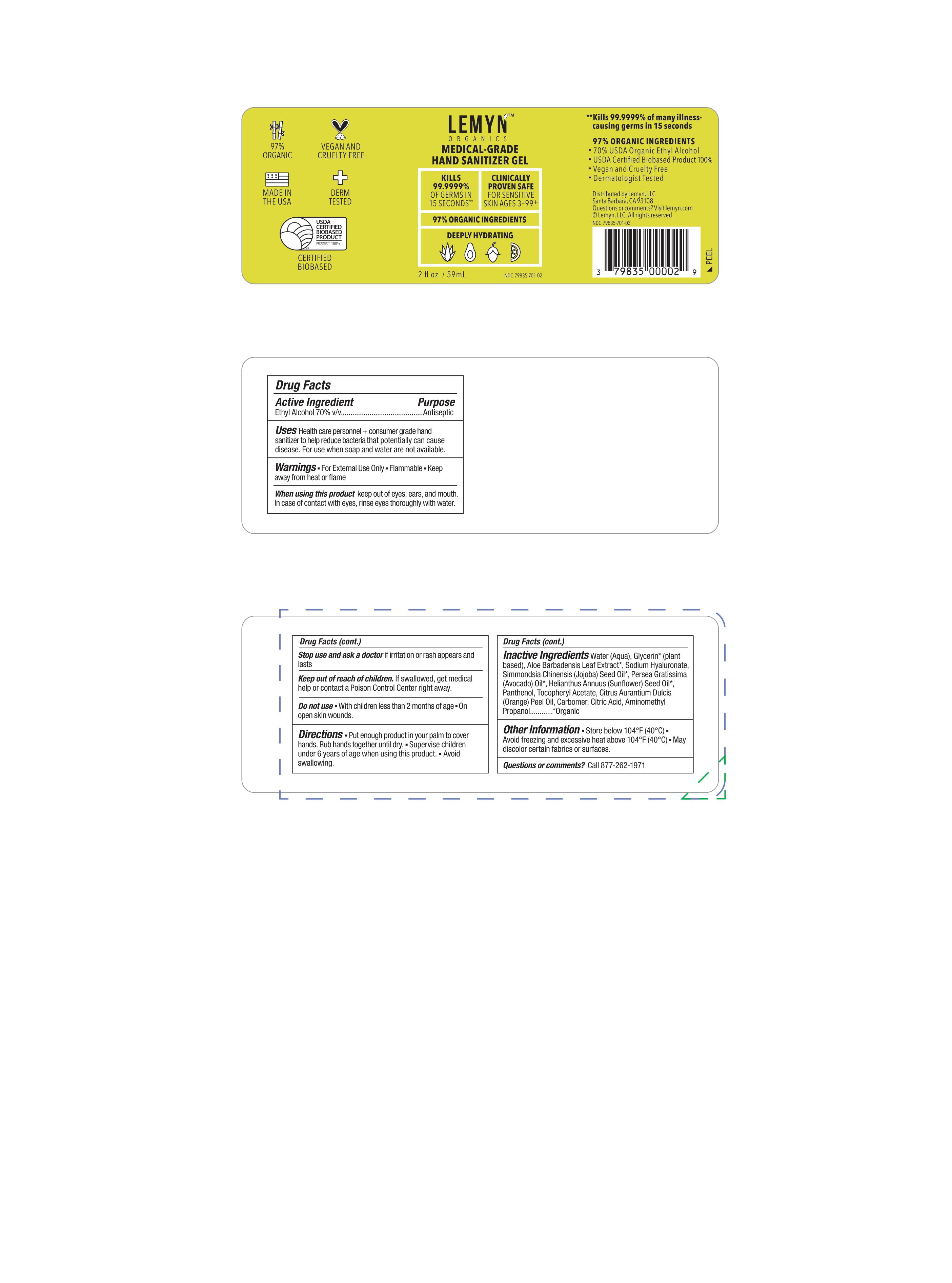 DRUG LABEL: Lemyn Organics Medical Grade Hand Sanitizer Gel
NDC: 67923-101 | Form: GEL
Manufacturer: Vege Labs LLC.
Category: otc | Type: HUMAN OTC DRUG LABEL
Date: 20210407

ACTIVE INGREDIENTS: ALCOHOL 70 mL/100 mL
INACTIVE INGREDIENTS: HYALURONATE SODIUM 0.001 mL/100 mL; JOJOBA OIL 0.001 mL/100 mL; AMINOMETHYL PROPANEDIOL 0.04275 mL/100 mL; WATER 28.28725 mL/100 mL; GLYCERIN 1.0075 mL/100 mL; ALOE VERA LEAF 0.0025 mL/100 mL; SUNFLOWER OIL 0.001 mL/100 mL; .ALPHA.-TOCOPHEROL ACETATE 0.001 mL/100 mL; CARBOMER 940 0.33 mL/100 mL; ORANGE OIL, COLD PRESSED 0.3 mL/100 mL; AVOCADO OIL 0.001 mL/100 mL; PANTHENOL 0.025 mL/100 mL

Lemyn Hand Sanitizer 2 fl oz

Active Ingredient

-

Active Ingredient

Ethyl Alcohol 70% v/v

Purpose

Antiseptic

Uses

Health care personnel + consumer grade hand sanitizer to help reduce bacteria that potentially can cause disease. For use when soap and water are not available.

Warnings

- For External Use Only
- Flammable
- Keep away from heat or flame

When using this product

keep out of eyes, ears, and mouth. In case of contact with eyes, rinse eyes thoroughly with water.

Stop use and ask a doctor

if irritation or rash appears and lasts

Keep out of reach of children.

If swallowed, get medical help or contact a Poison Control Center right away.

Do not use

- With children less than 2 months of age
- On open skin wounds

Directions

- Put enough product in your palm to cover hands. Rub hands together until dry.
- Supervise children under 6 years of age when using this product.
- Avoid swallowing.

Inactive Ingredients

JOJOBA OIL (UNII: 724GKU717M)

CITRIC ACID MONOHYDRATE (UNII: 2968PHW8QP)

.ALPHA.-TOCOPHEROL ACETATE (UNII: 9E8X80D2L0)

ORANGE OIL (UNII: AKN3KSD11B)

AMINOMETHYLPROPANOL (UNII: LU49E6626Q)

GLYCERIN (UNII: PDC6A3C0OX)

ALOE VERA LEAF (UNII: ZY81Z83H0X)

HYALURONATE SODIUM (UNII: YSE9PPT4TH)

CARBOMER HOMOPOLYMER, UNSPECIFIED TYPE (UNII: 0A5MM307FC)

COMFREY ROOT (UNII: M9VVZ08EKQ)

SUNFLOWER OIL (UNII: 3W1JG795YI)

PANTHENOL (UNII: WV9CM0O67Z)

AVOCADO OIL (UNII: 6VNO72PFC1)

WATER (UNII: 059QF0KO0R)

Other Information

- Store below 104F (40C)
- Avoid freezing and excessive heat above 104F (40C)
- May discolor certain fabrics or sufaces.

Questions and Comments?

Call 877-262-1971

Dosage and Administration

Put enough product in your palm to cover hands. Rub hands together until dry.

Supervise children under 6 years of age when using this product.
Avoid swallowing.

Indications and Usage

Hand sanitizer to help reduce bacteria that potentially can cause disease. For use when soap and water are not available

Put enough product in your palm to cover hands. Rub hands together until dry.
Supervise children under 6 years of age when using this product.
Avoid swallowing.

2 fl oz Label

59 mL NDC: 67923-101-02

COMPANY INFORMATION

Distributed by Lemyn, LLC

Santa Barbara, CA 93108

Questions or comments?

Visit lemyn.com